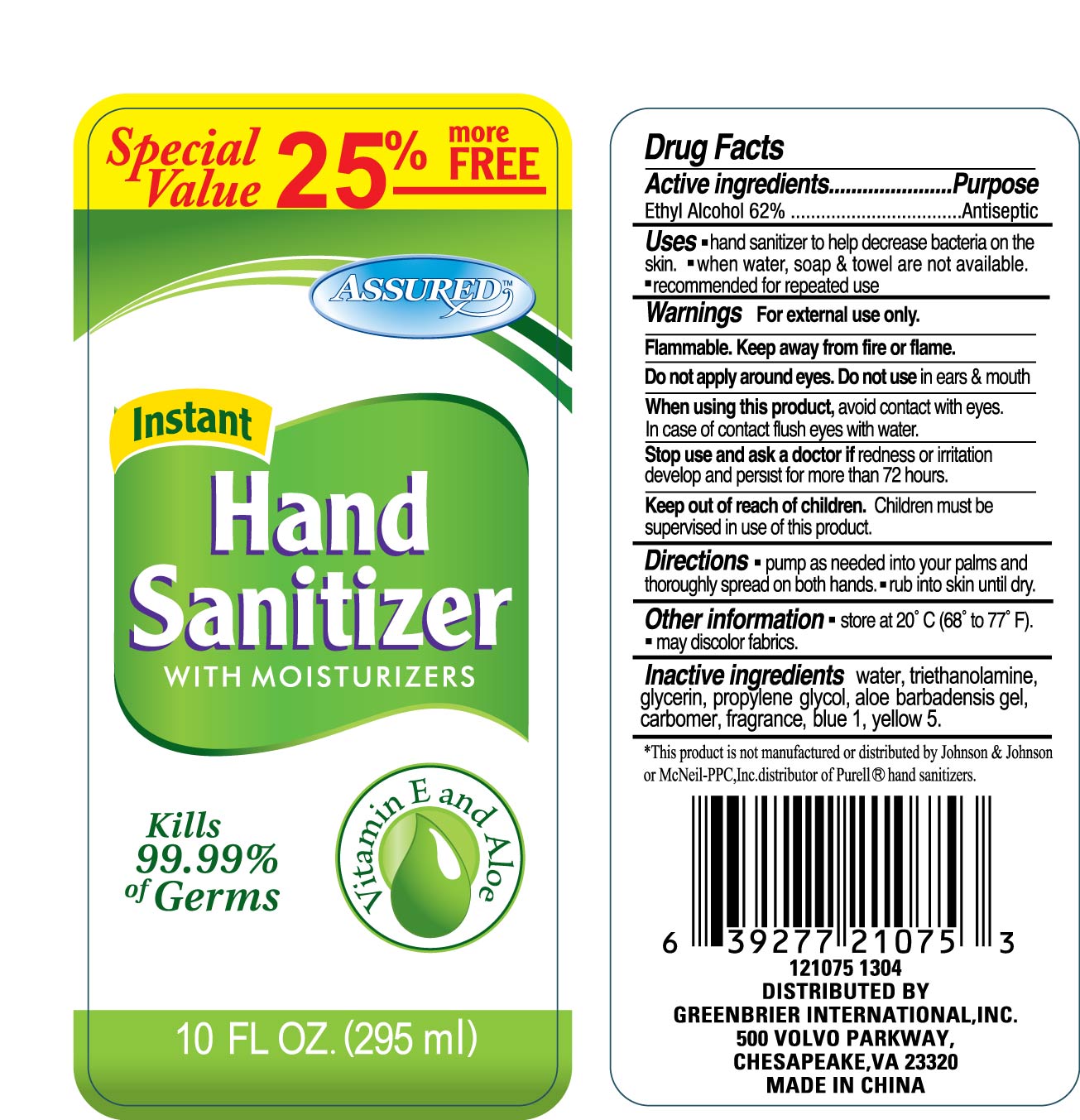 DRUG LABEL: Instant Hand Sanitizer With Moisturizers (Vitamin E and Aloe)
NDC: 33992-1411 | Form: GEL
Manufacturer: Greenbrier International
Category: otc | Type: HUMAN OTC DRUG LABEL
Date: 20121127

ACTIVE INGREDIENTS: alcohol 62 mL/100 mL
INACTIVE INGREDIENTS: Water; TROLAMINE; GLYCERIN; PROPYLENE GLYCOL; .ALPHA.-TOCOPHEROL ACETATE, D-; ALOE VERA LEAF; CARBOMER 934

Drug Fact

Active Ingredient Purpose
Alcohol 62% ********** Antiseptic

PURPOSE

Hand sanitizer to help decrease bacteria on the skin.
when water, soap and towel are not available
Recommended for repeat use

KEEP OUT OF REACH OF CHILDREN

Children must be supervised in use of this product.

INDICATIONS AND USAGE

Pump as needed into your palms and thoroughly spread on both hands.
Rub into skin until dry.

WARNINGS

For external use only.
Flammable, keep away from fire or flame.
Do not apply around eyes; Do not use in ears and mouth.
When using this products, avoid contact with eyes. In case of contact, flush eyes with water.
Stop use and ask a doctor, if redness or irritation develop and persist for more than 72 hours.

DOSAGE AND ADMINISTRATION

Pump as needed into your palms and thoroughly spread on both hands.
Rub into skin until dry.

INACTIVE INGREDIENT

Water, triethanolamine, glycerin, propylene glycol, gtocopheryl acetate, aloe barbadensis gel, carbomer, fragrance